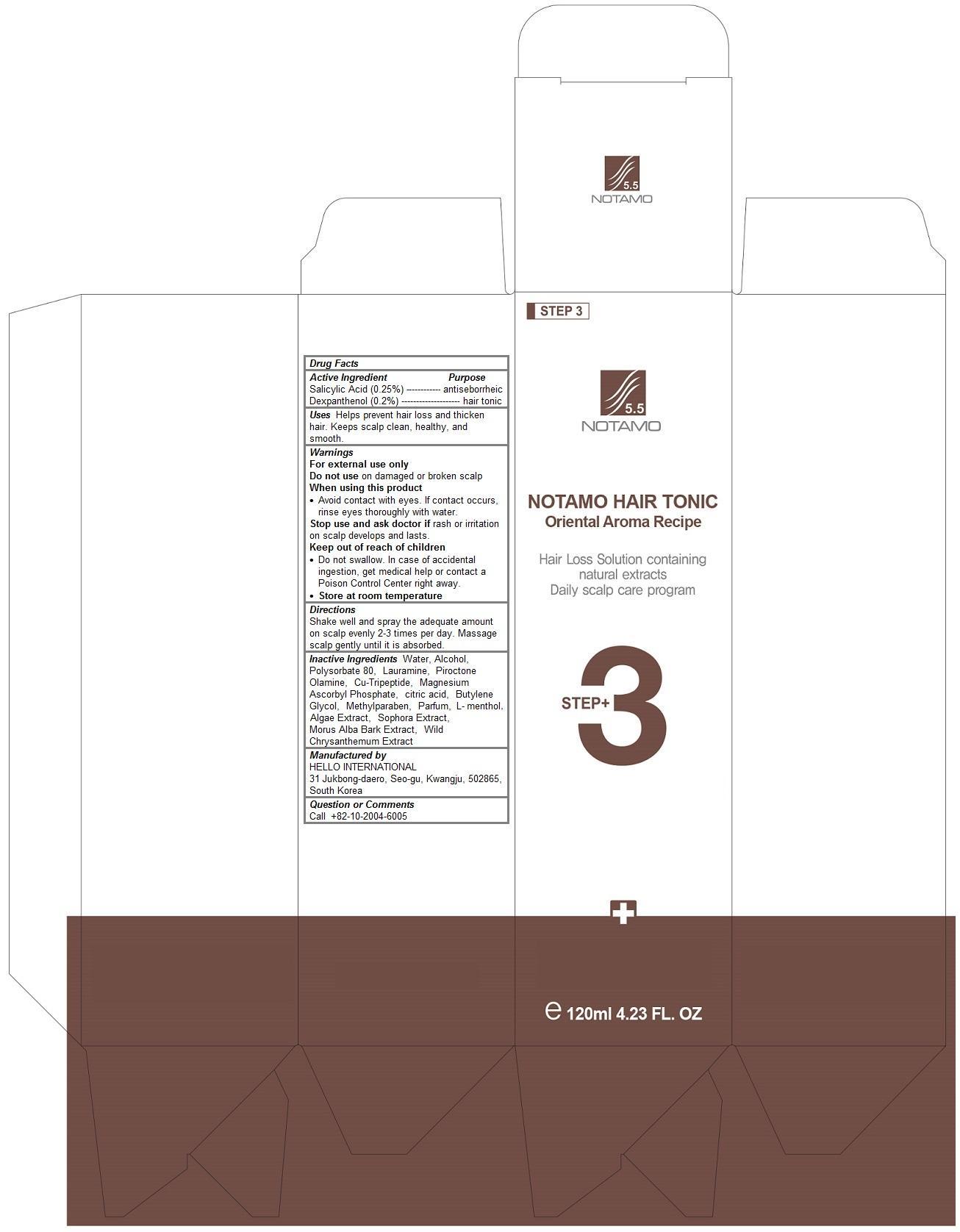 DRUG LABEL: Notamo Hair Tonic
NDC: 69709-102 | Form: LIQUID
Manufacturer: HELLO INTERNATIONAL
Category: otc | Type: HUMAN OTC DRUG LABEL
Date: 20150408

ACTIVE INGREDIENTS: DEXPANTHENOL 0.2 1/120 mL; SALICYLIC ACID 0.25 1/120 mL
INACTIVE INGREDIENTS: WATER; Alcohol; Polysorbate 80; DODECYLAMINE; PIROCTONE OLAMINE; Magnesium Ascorbyl Phosphate; CITRIC ACID MONOHYDRATE; Butylene Glycol; Methylparaben; LEVOMENTHOL; SOPHORA FLAVESCENS ROOT

Notamo Hair Tonic